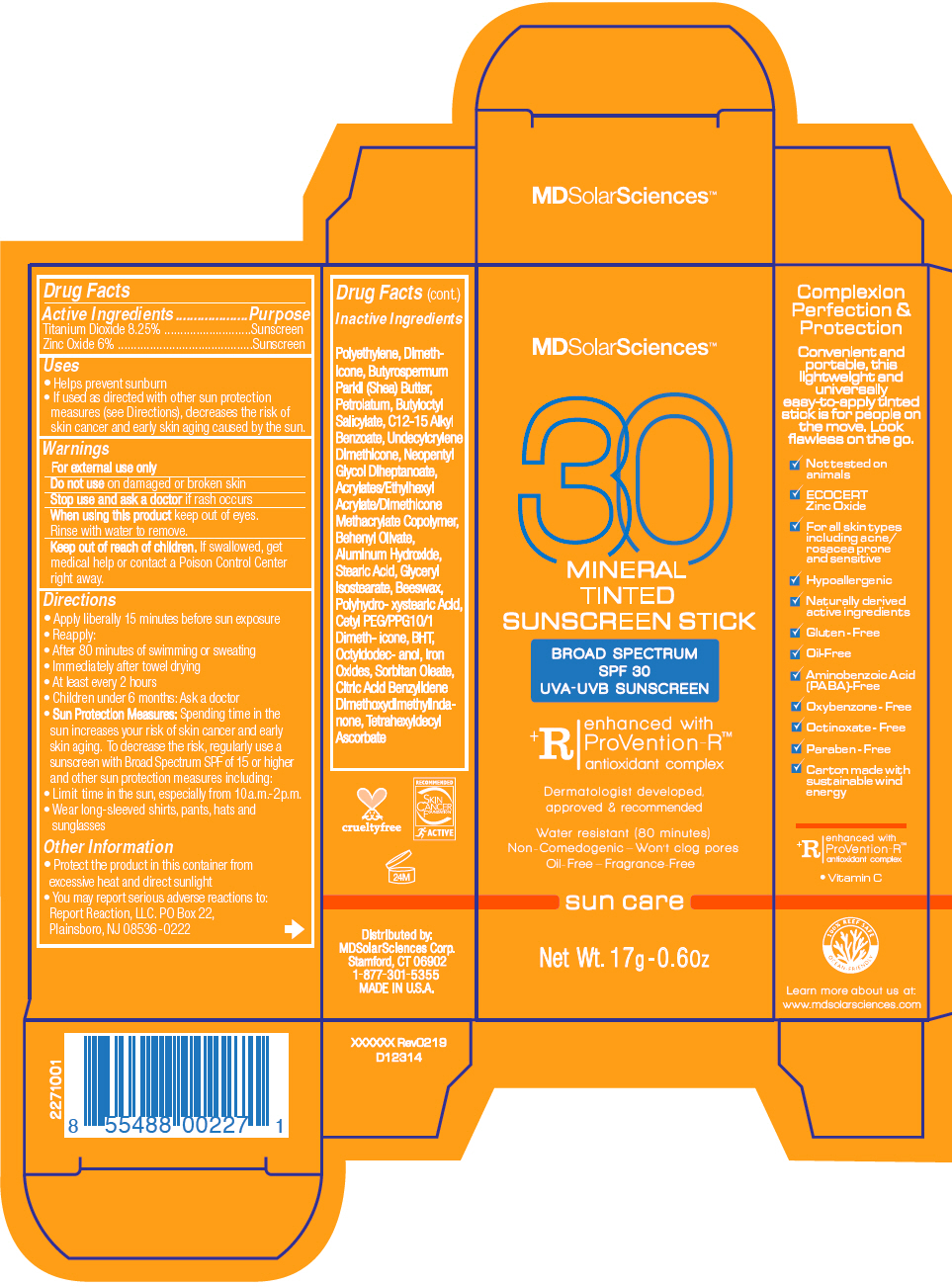 DRUG LABEL: Mineral Tinted Sunscreen 
NDC: 49358-563 | Form: STICK
Manufacturer: MDSolarSciences
Category: otc | Type: HUMAN OTC DRUG LABEL
Date: 20190805

ACTIVE INGREDIENTS: Titanium Dioxide 0.96 g/12 g; Zinc Oxide 0.792 g/12 g
INACTIVE INGREDIENTS: HIGH DENSITY POLYETHYLENE; Dimethicone; SHEA BUTTER; PETROLATUM; BUTYLOCTYL OLEATE; SALICYLIC ACID; ALKYL (C12-15) BENZOATE; NEOPENTYL GLYCOL DIHEPTANOATE; BEHENYL OLIVATE; ALUMINUM HYDROXIDE; STEARIC ACID; GLYCERYL ISOSTEARATE; YELLOW WAX; POLYHYDROXYSTEARIC ACID (2300 MW); CETYL PEG/PPG-10/1 DIMETHICONE (HLB 2); BUTYLATED HYDROXYTOLUENE; BENZYLIDENE DIMETHOXYDIMETHYLINDANONE; TETRAHEXYLDECYL ASCORBATE; FERRIC OXIDE RED; FERRIC OXIDE YELLOW; FERROSOFERRIC OXIDE

Mineral Tinted Sunscreen Stick
Broad Spectrum SPF 30 Sunscreen UVA-UVB Sunscreen

Drug Facts

ACTIVE INGREDIENT

Active Ingredients | Purpose
Titanium Dioxide 8.25% | Sunscreen
Zinc Oxide 6% | Sunscreen

Uses

- Helps prevent sunburn
- If used as directed with other sun protection measures (see Directions), decreases the risk of skin cancer and early skin aging caused by the sun.

Warnings

For external use only

Do not use on damaged or broken skin

Stop use and ask a doctor if rash occurs

When using this product keep out of eyes. Rinse with water to remove.

Keep out of reach of children. If swallowed, get medical help or contact a Poison Control Center right away.

Directions

- Apply liberally 15 minutes before sun exposure
- Reapply:
- After 80 minutes of swimming or sweating
- Immediately after towel drying
- At least every 2 hours
- Children under 6 months: Ask a doctor
- Sun Protection Measures: Spending time in the sun increases your risk of skin cancer and early skin aging. To decrease the risk, regularly use a sunscreen with Broad Spectrum SPF of 15 or higher and other sun protection measures including:
- Limit time in the sun, especially from 10a.m.-2p.m.
- Wear long-sleeved shirts, pants, hats and sunglasses

Other Information

- Protect the product in this container from excessive heat and direct sunlight
- You may report serious adverse reactions to: Report Reaction, LLC. PO Box 22, Plainsboro, NJ 08536-0222

Inactive Ingredients

Polyethylene, Dimethicone, Butyrospermum Parkii (Shea) Butter, Petrolatum, Butyloctyl Salicylate, C12-15 Alkyl Benzoate, Undecylcrylene Dimethicone, Neopentyl Glycol Diheptanoate, Acrylates/Ethylhexyl Acrylate/Dimethicone Methacrylate Copolymer, Behenyl Olivate, Aluminum Hydroxide, Stearic Acid, Glyceryl Isostearate, Beeswax, Polyhydro- xystearic Acid, Cetyl PEG/PPG10/1 Dimeth- icone, BHT, Octyldodec- anol, Iron Oxides, Sorbitan Oleate, Citric Acid Benzylidene Dimethoxydimethylindanone, Tetrahexyldecyl Ascorbate

Distributed by:
MDSolarSciences Corp.
Stamford, CT 06902

PRINCIPAL DISPLAY PANEL - 17 g Tube Carton

MDSolarSciences™

30

MINERAL
TINTED
SUNSCREEN STICK

BROAD SPECTRUM
SPF 30
UVA-UVB SUNSCREEN

^+R
enhanced with
ProVention-R™
antioxidant complex

Dermatologists developed,
approved & recommended

Water resistant (80 minutes)
Non-Comedogenic – Won't clog pores
Oil-Free – Fragrance-Free

sun care

Net Wt. 17g -0.6Oz